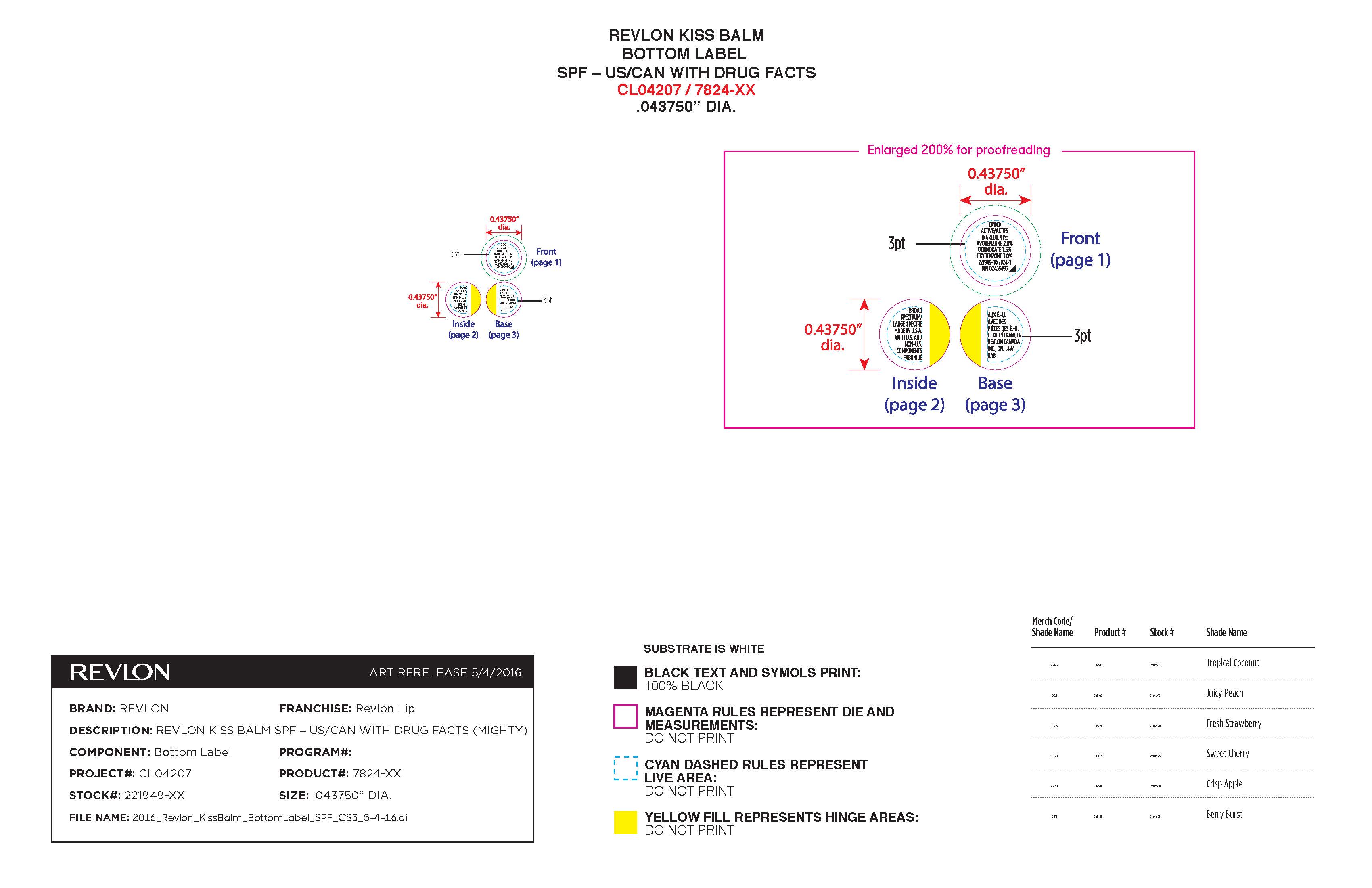 DRUG LABEL: Revlon Kiss Balm SPF 20
NDC: 10967-640 | Form: STICK
Manufacturer: Revlon Consumer Products Corp
Category: otc | Type: HUMAN OTC DRUG LABEL
Date: 20241231

ACTIVE INGREDIENTS: AVOBENZONE 2 g/1 mL; OCTINOXATE 7.5 g/1 mL; OXYBENZONE 3 g/1 mL
INACTIVE INGREDIENTS: LIMONENE, (+/-)-; BENZYL ALCOHOL; CITRAL; .ALPHA.-HEXYLCINNAMALDEHYDE; .ALPHA.-AMYLCINNAMALDEHYDE; HYDROXYCITRONELLAL; ISOMETHYL-.ALPHA.-IONONE; LINALOOL, (+/-)-; POLYBUTENE (1400 MW); DIISOSTEARYL MALATE; ISONONYL ISONONANOATE; BIS-DIGLYCERYL POLYACYLADIPATE-2; OCTYLDODECYL NEOPENTANOATE; HIGH DENSITY POLYETHYLENE; CERESIN; DIISOPROPYL DILINOLEATE; WHITE WAX; PUNICA GRANATUM SEED OIL; RASPBERRY SEED OIL; GRAPE SEED OIL; CALCIUM ALUMINUM BOROSILICATE; CANDELILLA WAX; CETYL PALMITATE; BENZOIC ACID; TRIS-BHT MESITYLENE; SILICON DIOXIDE; SACCHARIN SODIUM; BENZYL BENZOATE

Revlon Kiss Balm SPF 20

Active Ingredients:

Avobenzone 2.0%

Octinoxate 7.5%

Oxybenzone 3.0%

Inactive Ingredients

Polybutene, Diisostearyl Malate, Isononyl Isononanoate, Bis-Diglyceryl Polyacyladipate-2, Octyldodecyl Neopentanoate, Polyethylene, Ozokerite, Diisopropyl Dimer Dilinoleate, Cera Alba ((Beeswax) Cire D Abeille), Parfum (Fragrance), Flavor, Punica Granatum Seed Oil, Rubus Idaeus (Raspberry) Seed Oil, Vitis Vinifera (Grape) Seed Oil, Calcium Aluminum Borosilicate, Euphorbia Cerifera (Candelilla) Wax, Cetyl Palmitate, Benzoic Acid, Oxidized Polyethylene, BHT, Silica, Sodium Saccharin, Benzyl Benzoate, Limonene, Benzyl Alcohol, Citral, Amyl Cinnamal, Hexyl Cinnamal, Hydroxycitronellal, Alpha-Isomethyl Ionone, Linalool

May Contain- Mica, Titanium Dioxide (CI 77891), Iron Oxides (CI 77491, 77492, 77499), Red 6 Lake (CI 15850), Red 7 Lake (CI 15850), Red 28 Lake (CI 45410), Red 33 Lake (CI 17200), Blue 1 Lake (CI 42090), Yellow 5 Lake (CI 19140), Yellow 6 Lake (CI 15985), Carmine (CI 75470

EXTERNAL USE ONLY

Questions?

1-800-473-8566

DOSAGE AND ADMINISTRATION

Apply liberally 15 minutes before sun exposure.

INDICATIONS AND USAGE

Helps prevent sunbunrs. If used as directed with other sun protection measures (See Directions), decreases the risk of skin cancer and early skin aging caused by the sun.

PURPOSE

Sunscreen

KEEP OUT OF REACH OF CHILDREN

Keep out of the reach of children. If product is swallowed, get medical help or contact a Poison Control Center right away.

Product Label

Revlon Kiss Balm SPF 20

Broad Spectrum

Avobenzone- 2.0%

Octinoxate - 7.5%

Oxybenzone- 3.0%